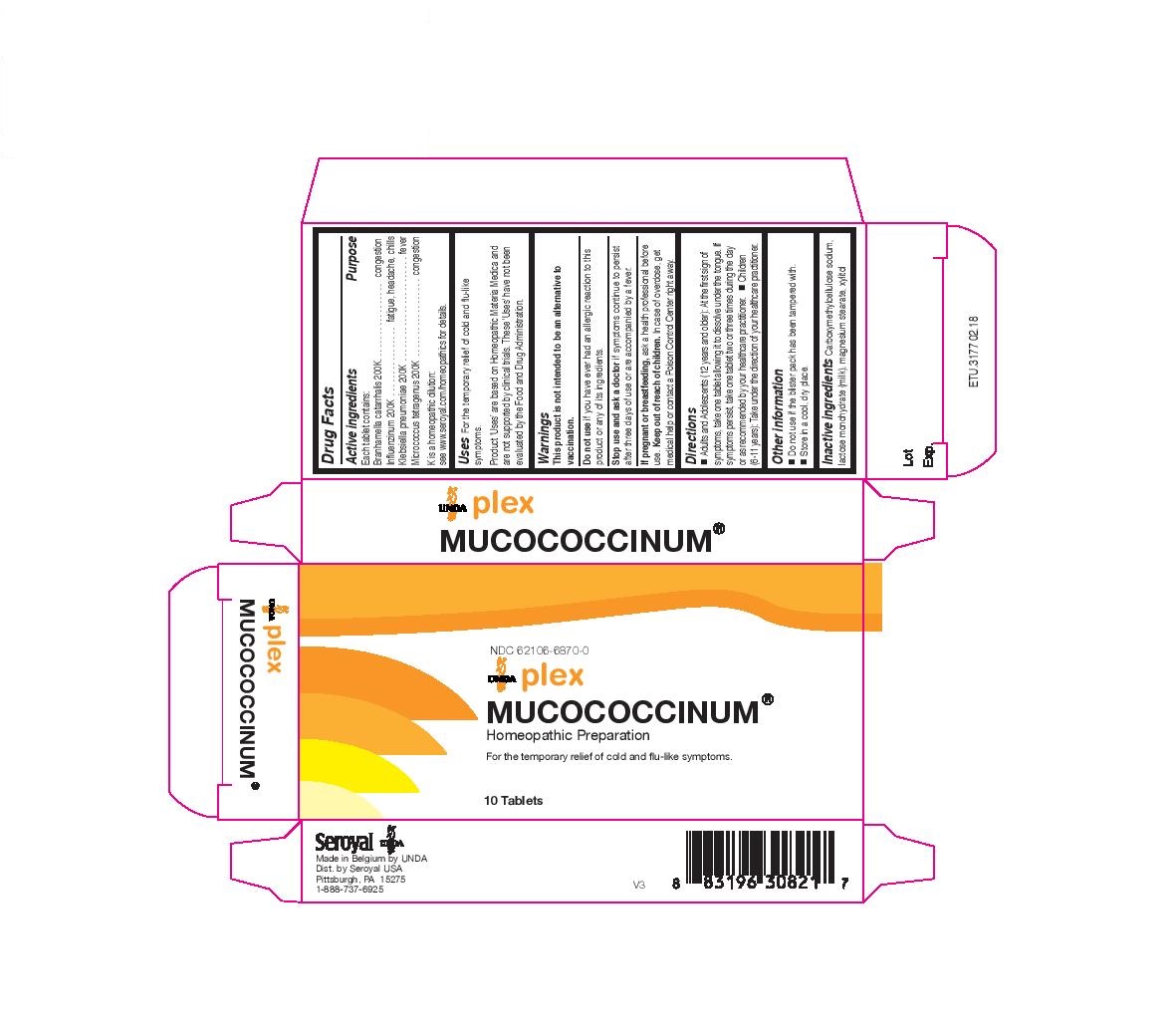 DRUG LABEL: Muco coccinum
NDC: 62106-6870 | Form: TABLET
Manufacturer: Seroyal USA
Category: homeopathic | Type: HUMAN OTC DRUG LABEL
Date: 20221109

ACTIVE INGREDIENTS: ANAEROCOCCUS TETRADIUS 200 [hp_C]/1 1; INFLUENZA A VIRUS 200 [hp_C]/1 1; INFLUENZA B VIRUS 200 [hp_C]/1 1; KLEBSIELLA PNEUMONIAE 200 [hp_C]/1 1; MORAXELLA CATARRHALIS SUBSP. CATARRHALIS 200 [hp_C]/1 1
INACTIVE INGREDIENTS: CROSCARMELLOSE SODIUM; LACTOSE; MAGNESIUM STEARATE; XYLITOL

Mucococcinum

Active ingredients

Each tablet contains:
Branhamella catarrhalis 200K
Influenzinum 200K
Klebsiella pneumoniae 200K
Micrococcus tetragenus 200K

Uses

For the temporary relief of cold and flu-like symptoms

Warnings
This product is not intended to be an alternative to
vaccination.
Do not use if you have ever had an allergic reaction to this
product or any of its ingredients.
Stop use and ask a doctor if symptoms continue to persist
after three days of use or are accompanied by a fever.
If pregnant or breastfeeding, ask a health professional before
use. Keep out of reach of children. In case of overdose, get
medical help or contact a Poison Control Center right away.

Do not use if you have ever had an allergic reaction to this product or any of its ingredients.

PREGNANCY OR BREAST FEEDING

If pregnant or breastfeeding, ask a health professional before use.

Keep out of reach of children.

OVERDOSAGE

In case of overdose, get medical help or contact a Poison Control Center right away.

Inactive ingredients

Carboxymethylcellulose sodium, lactose monohydrate (milk), magnesium stearate, xylitol

Other information
Do not use if the blister pack has been tampered with.
Store in a cool, dry place.

Directions
Adults and Adolescents (12 years and older): At the first sign of symptoms, take one tablet allowing it to dissolve under the tongue. If
symptoms persist, take one tablet two or three times during the day or as recommended by your healthcare practitioner.

Children (6-11 years): Take under the direction of your healthcare practitioner.

Uses

For the temporary relief of cold and flu-like symptoms.

Directions
Adults and Adolescents (12 years and older): At the first sign of symptoms, take one tablet allowing it to dissolve under the tongue. If
symptoms persist, take one tablet two or three times during the day or as recommended by your healthcare practitioner.

Children (6-11 years): Take under the direction of your healthcare practitioner.

PACKAGE LABEL

NDC 62106-6870-0

UNDA plex

MUCOCOCCINUM

Homeopathic Preparation

For the temporary relief of cold and flu-like symptoms.

10 Tablets